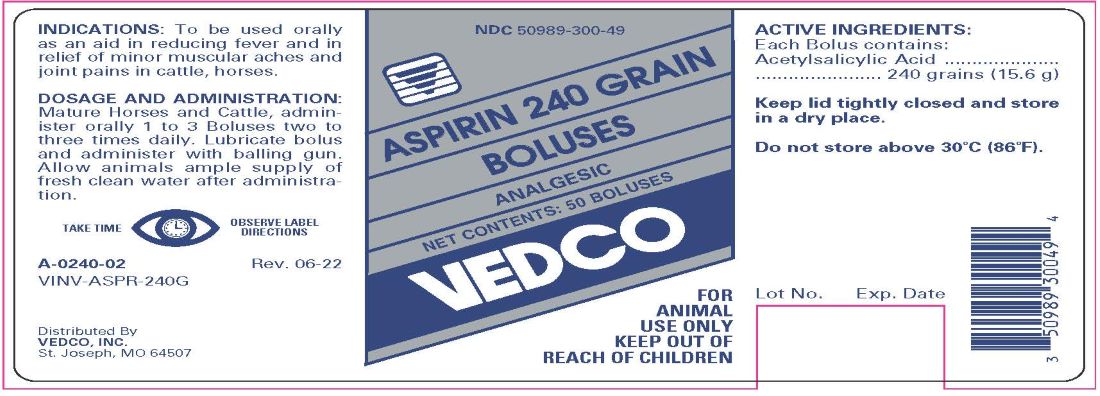 DRUG LABEL: ASPIRIN 
NDC: 50989-300 | Form: TABLET
Manufacturer: Vedco, Inc.
Category: animal | Type: OTC ANIMAL DRUG LABEL
Date: 20230817

ACTIVE INGREDIENTS: ASPIRIN 15.6 g/1 1

ASPIRIN 240 GRAIN BOLUSES ANALGESIC

INDICATIONS

To be used orally as an aid in reducing fever and in relief of minor muscular aches and joint pains in cattle, horses.

DOSAGE AND ADMINISTRATION

Mature Horses and Cattle, administer orally 1 to 3 Boluses two to three times daily. Lubricate bolus and administer with balling gun. Allow animals ample supply of fresh clean water after administration.

CONTENTS

ACTIVE INGREDIENTS:

Each Bolus contains:
Acetylsalicylic Acid...........................240 grains (15.6 g)

STORAGE AND HANDLING

Keep lid tightly closed and store in a dry place.

Do not store above 30oC (86oF).

TAKE TIME OBSERVE LABEL DIRECTIONS